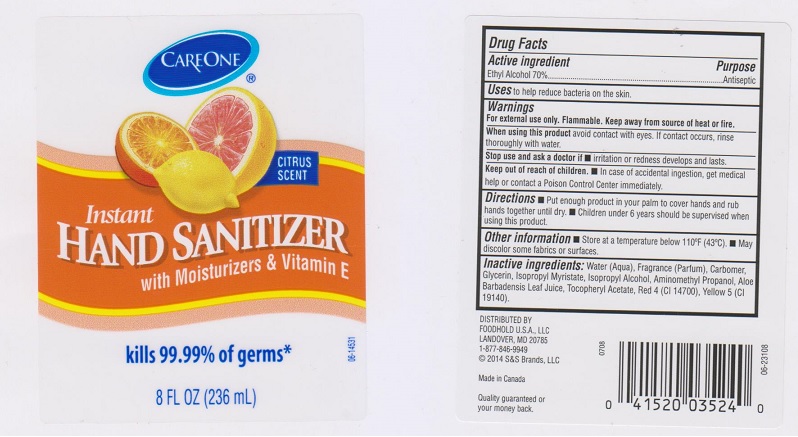 DRUG LABEL: Care One
NDC: 41520-042 | Form: LIQUID
Manufacturer: American Sales Company
Category: otc | Type: HUMAN OTC DRUG LABEL
Date: 20170518

ACTIVE INGREDIENTS: ALCOHOL 700 mg/1 mL
INACTIVE INGREDIENTS: WATER; CARBOMER 934; GLYCERIN; ISOPROPYL MYRISTATE; ISOPROPYL ALCOHOL; AMINOMETHYLPROPANOL; ALOE VERA LEAF; .ALPHA.-TOCOPHEROL ACETATE, DL-; FD&C RED NO. 4; FD&C YELLOW NO. 5

Drug Facts

Active ingredient

Ethyl Alcohol 70%

Purpose

Antiseptic

Uses

to help reduce bacteria on the skin.

Warnings

For external use only. Flammable. Keep away from source of heat or fire.

When using this product

avoid contact with eyes. If contact occurs, rinse thoroughly with water.

Stop use and ask a doctor if

- irritation or redness develops and lasts.

Keep out of reach of children.

- In case of accidental ingestion, get medical help or contact a Poison Control Center immediately.

Directions

- Put enough product in your palm to cover hands and rub hands together until dry.
- Children under 6 years should be supervised when using this product.

Other information

- store at a temperature below 110°F (43°C).
- May discolor some fabrics or surfaces.

Inactive ingredients

Water (Aqua), Fragrance (Parfum), Carbomer, Glycerin, Isopropyl Myristate, Isopropyl Alcohol, Aminomethyl Propanol, Aloe Barbadensis Leaf Juice, Tocopheryl Acetate, Red 4 (CI 14700), Yellow 5 (CI 19140).